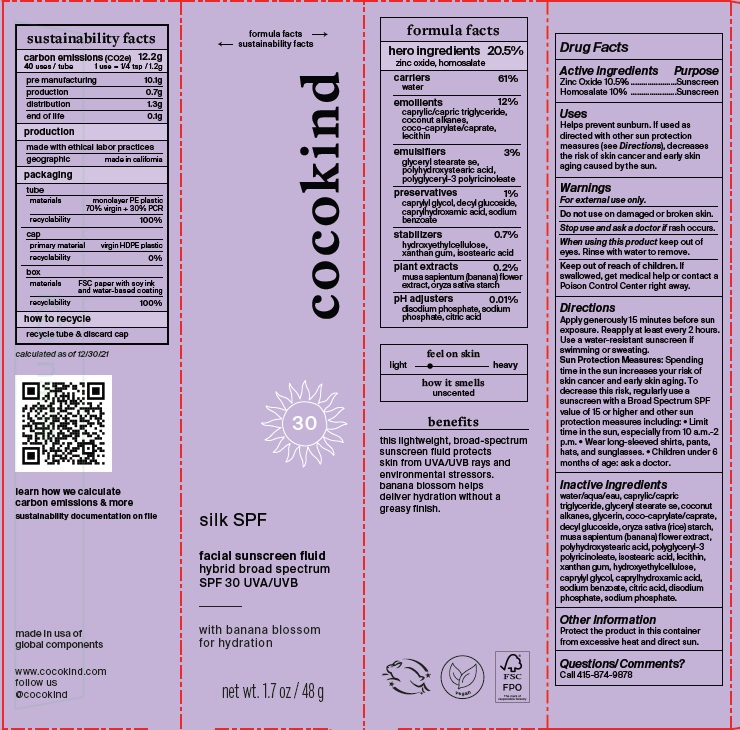 DRUG LABEL: silk SPF facial sunscreen fluid hybrid broad spectrum SPF 30 UVA/UVB
NDC: 79356-202 | Form: CREAM
Manufacturer: OneKind.25
Category: otc | Type: HUMAN OTC DRUG LABEL
Date: 20250612

ACTIVE INGREDIENTS: ZINC OXIDE 10.5 g/100 g; HOMOSALATE 10 g/100 g
INACTIVE INGREDIENTS: COCO-CAPRYLATE/CAPRATE; MUSA X PARADISIACA FLOWER; WATER; MEDIUM-CHAIN TRIGLYCERIDES; GLYCERYL STEARATE SE; POLYHYDROXYSTEARIC ACID (2300 MW); SODIUM PHOSPHATE, DIBASIC, ANHYDROUS; SODIUM PHOSPHATE; HYDROXYETHYL CELLULOSE, UNSPECIFIED; CAPRYLYL GLYCOL; CAPRYLHYDROXAMIC ACID; COCONUT ALKANES; GLYCERIN; DECYL GLUCOSIDE; CITRIC ACID MONOHYDRATE; POLYGLYCERYL-3 PENTARICINOLEATE; ISOSTEARIC ACID; LECITHIN, SOYBEAN; XANTHAN GUM; SODIUM BENZOATE; STARCH, RICE

silk SPF facial sunscreen fluid hybrid broad spectrum SPF 30 UVA/UVB

Active Ingredients

Zinc Oxide 10.5%

Homosalate 10%

Purpose

Sunscreen

Uses
Helps prevent sunburn. If used as
directed with other sun protection
measures (see Directions), decreases
the risk of skin cancer and early skin
aging caused by the sun.

Warnings
For external use only.

Do not use on damaged or broken skin.

When using this product keep out of
eyes. Rinse with water to remove.

Stop use and ask a doctor if rash occurs.

Keep out of reach of children. If
swallowed, get medical help or contact a
Poison Control Center right away.

Directions
Apply generously 15 minutes before sun
exposure. Reapply at least every 2 hours.
Use a water-resistant sunscreen if
swimming or sweating.

OTHER SAFETY INFORMATION

Sun Protection Measures: Spending
time in the sun increases your risk of
skin cancer and early skin aging. To
decrease this risk, regularly use a
sunscreen with a Broad Spectrum SPF
value of 15 or higher and other sun
protection measures including: Limit
time in the sun, especially from 10 a.m.- 2
p.m. Wear long-sleeved shirts, pants,
hats, and sunglasses. Children under 6
months of age: ask a doctor.

Inactive Ingredients
water/aqua/eau, caprylic/capric
triglyceride, glyceryl stearate se, coconut
alkanes, glycerin, coco-caprylate/caprate,
decyl glucoside, oryza sativa (rice) starch,
musa sapientum (banana) flower extract,
polyhydroxystearic acid, polyglyceryl-3
polyricinoleate, isostearic acid, lecithin,
xanthan gum, hydroxyethylcellulose,
caprylyl glycol, caprylhydroxamic acid,
sodium benzoate, citric acid, disodium
phosphate, sodium phosphate.